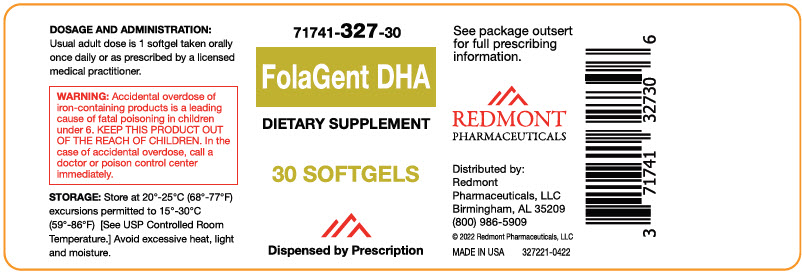 DRUG LABEL: FolaGent DHA
NDC: 71741-327 | Form: CAPSULE, GELATIN COATED
Manufacturer: Redmont Pharmaceuticals, LLC
Category: other | Type: DIETARY SUPPLEMENT
Date: 20220427

ACTIVE INGREDIENTS: BETA CAROTENE 600 ug/1 1; Vitamin A Palmitate 600 ug/1 1; Ascorbic Acid 60 mg/1 1; Cholecalciferol 10 ug/1 1; .ALPHA.-TOCOPHEROL, D- 20.1 mg/1 1; THIAMINE MONONITRATE 1.7 mg/1 1; Riboflavin 2 mg/1 1; Niacinamide 20 mg/1 1; Pyridoxine Hydrochloride 2.5 mg/1 1; Folic Acid 1000 ug/1 1; Cyanocobalamin 8 ug/1 1; Biotin 300 ug/1 1; Calcium Pantothenate 10 mg/1 1; Calcium Carbonate 200 mg/1 1; Iron 28 mg/1 1; Potassium Iodide 150 ug/1 1; Magnesium Oxide 50 mg/1 1; Zinc Oxide 15 mg/1 1; Cupric Oxide 2 mg/1 1; Fish Oil 235 mg/1 1
INACTIVE INGREDIENTS: Gelatin Type B Bovine (150 Bloom); Glycerin; Yellow Wax; Water; Lecithin, Soybean; Annatto

FolaGent DHA

HEALTH CLAIM

71741-327-30
Multivitamin
Dietary Supplement
Dispensed by Prescription [This product is a prescription-folate with or without other dietary ingredients that – due to increased folate levels increased risk associated with masking B12 deficiency (pernicious anemia) requires administration under the care of a licensed medical practitioner (64 FR 8760). 1-3 The most appropriate way to ensure pedigree reporting consistent with these regulatory guidelines and safety monitoring is to dispense this product only by prescription. This is not an Orange Book product. This product may be administered only under a physician's supervision and all prescriptions using this product shall be pursuant to state statutes as applicable. The ingredients, indication or claims of this product are not to be construed to be drug claims.]

STATEMENT OF IDENTITY

Supplement Facts
Serving Size: 1 Softgel
Serving Per Container:
 | Amount Per Serving | % Daily Value
Calories | 5
Total Fat | 0.5 g | <1%
Cholesterol | 25 mg | 8%
Vitamin A (50% Beta-Carotene, 50% Retinyl Palmitate) | 1200 mcg RAE (4000 IU) | 133%
Vitamin C (as Ascorbic Acid) | 60 mg | 67%
Vitamin D (as Cholecalciferol) | 10 mcg | 50%
Vitamin E (as d-Alpha Tocopherol) | 20.1 mg (30 IU) | 134%
Thiamin (B1) (from Thiamine Mononitrate) | 1.7 mg | 142%
Riboflavin (B2) | 2 mg | 154%
Niacin (as Niacinamide) | 20 mg | 125%
Vitamin B6 (from Pyridoxine Hydrochloride) | 2.5 mg | 147%
Folate (1000 mcg Folic Acid) | 1700 mcg DFE | 425%
Vitamin B12 (as Cyanocobalamin) | 8 mcg | 333%
Biotin | 300 mcg | 1000%
Pantothenic Acid (from d-Calcium Pantothenate) | 10 mg | 200%
Calcium (from Calcium Carbonate) | 200 mg | 15%
Iron (from Carbonyl Iron) | 28 mg | 156%
Iodine (from Potassium Iodide) | 150 mcg | 100%
Magnesium (from Magnesium Oxide) | 50 mg | 12%
Zinc (from Zinc Oxide) | 15 mg | 136%
Cooper (Cooper Oxide) | 2 mg | 222%
Eicosapentaenoic Acid (as EE) (from Fish Oil) | 200 mg | [Daily Values not established]
Docosahexaenoic Acid (as EE) (from Fish Oil) | 35 mg

Other Ingredients: Bovine Gelatin, Glycerin, Yellow Beeswax, Purified Water, Soy Lecithin, Annatto.

Allergens: Fish (Anchovy, Sardine, Tuna), Soy.

Does Not Contain: Peanuts, Tree Nuts, Shellfish, Eggs, Milk, Wheat.

INDICATIONS

FolaGent DHA is prescription dietary supplement formulated for the clinical dietary management of suboptimal nutritional status in patients where advanced folate supplementation is required and nutritional supplementation in physiologically stressful conditions for maintenance of good health.

FolaGent DHA is formulated as a prescription dietary supplement for use in the dietary management of patients with nutritional deficiencies or are in need of nutritional supplementation.

CONTRAINDICATIONS

This product is contraindicated in patients with a known hypersensitivity to any of the ingredients.

PRECAUTIONS

Folic acid alone is improper therapy in the treatment of pernicious anemia and other megaloblastic anemias where Vitamin B12 is deficient. Folic acid in doses above 1.0 mg daily may obscure pernicious anemia in that hematologic remission can occur while neurological manifestations progress.

WARNINGS

WARNING: Ingestion of more than 3 grams of omega-3 fatty acids (such as DHA) per day has been shown to have potential antithrombotic effects, including an increased bleeding time and International Normalized Ratio (INR). Administration of omega-3 fatty acids should be avoided in patients taking anticoagulants and in those known to have an inherited or acquired predisposition to bleeding.

WARNING: Accidental overdose of iron-containing products is a leading cause of fatal poisoning in children under 6. Keep this product out of reach of children. In case of accidental overdose, call a doctor or poison control center immediately.

ADVERSE REACTIONS

Allergic sensitization has been reported following both oral and parenteral administration of folic acid.

You should call your doctor for medical advice about serious adverse events. To report adverse side effects or to obtain product information, contact Redmont Pharmaceuticals, LLC at 1-800-986-5909.

DOSAGE AND ADMINISTRATION

Usual adult dose is 1 softgel taken orally once daily or as prescribed by a licensed medical practitioner.

HOW SUPPLIED

Child-resistant bottles of 30 softgels (71741-327-30 [Redmont Pharmaceuticals does not represent this product code to be National Drug Code (NDC). Product codes are formatted according to standard industry practice, to meet the formatting requirement by pedigree reporting and supply-chain control including pharmacies.]). Softgel is oblong shaped and orange reddish in color with possible dark spots.

1. Federal Register Notice of August 2, 1973 (38 FR 20750)
2. Federal Register Notice of October 17, 1980 (45 FR 69043, 69044)
3. Federal Register Notice of March 5, 1996 (61 FR 8760)

STORAGE AND HANDLING

STORAGE

Store at 20° - 25°C (68° - 77°F); excursions permitted to 15° - 30°C (59° - 86°F) [See USP Controlled Room Temperature.] Avoid excessive heat, light, and moisture.

TAMPER EVIDENT: Do not use if seal is broken or missing.

HEALTH CLAIM

Distributed by:
Redmont Pharmaceuticals, LLC
Birmingham, AL 35209
800-986-5909

These statements have not been evaluated by the Food and Drug Administration. This product is not intended to diagnose, treat, cure, or prevent any disease.

KEEP THIS AND ALL MEDICATIONS OUT OF THE REACH OF CHILDREN.

© 2022 Redmont Pharmaceuticals, LLC

327111-0422

PRINCIPAL DISPLAY PANEL - 30 Softgel Bottle Label

71741-327-30

FolaGent DHA

DIETARY SUPPLEMENT

30 SOFTGELS

Dispensed by Prescription